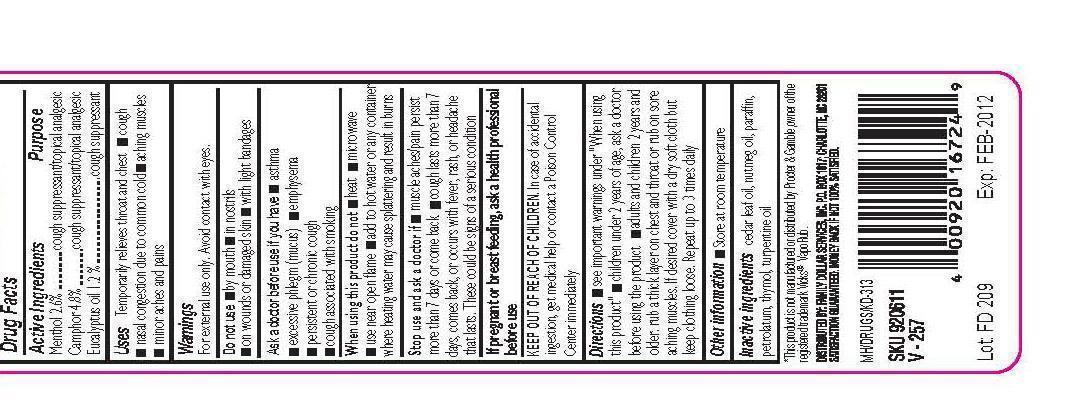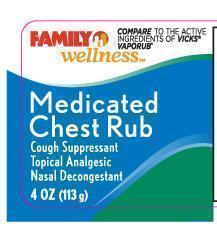 DRUG LABEL: Medicated
NDC: 55319-100 | Form: CREAM
Manufacturer: Family Dollar Services Inc
Category: otc | Type: HUMAN OTC DRUG LABEL
Date: 20121129

ACTIVE INGREDIENTS: CAMPHOR (SYNTHETIC) 4.8 g/100 g; MENTHOL 2.6 g/100 g; EUCALYPTUS OIL 1.2 g/100 g
INACTIVE INGREDIENTS: CEDAR LEAF OIL; NUTMEG OIL; PARAFFIN; PETROLATUM; THYMOL; TURPENTINE

Medicated chest rub

Active ingredients
Camphor 4.8%
Menthol 2.6%
Eucalyptus Oil 1.2%

Purpose

Cough suppressant /topical analgesic

Cough suppressant /topical analgesic

Cough supressan

INDICATIONS AND USAGE

Uses: Temporarily relieves throat and chest

- cough
- nasal congestion due to common cold
- aching muscles
- minor aches and pains

Warnings

For external use only. Avoid contact with eyes

Do not use:

- by mouth
- by nostrils
- on wounds or damaged skin
- with light bandages

Ask a doctor before use if you have

- asthma
- excessive phlem (mucus)
- emphysema
- persistent or chronic cough
- cough associated with smoking

When using this product do not heat

- microwave
- use near open flame
- add to hot water or any container where heating water may cause splattering and result in burns

Stop use and ask a doctor if

- muscle aches/pain persist more than more than 7 days or come back
- cough lasts more than 7 days, comes back, or occurs with fever, rash, or headache that lasts. These could be signs of a serious condition.

PREGNANCY OR BREAST FEEDING

If pregnant or breast feeding, ask a health profesional before use

Keep out reach of children.

In case of accidental ingestion get medical help or contact a Poison Control Center right away.

Directions

- see important warnings when using this product
- children under 2 years of age, ask a doctor before using this product
- adults and children 2 years older, rub a thick layer on chest and and throat or rub on sore,aching muscles. If desired cover with a dry soft cloth but keep clothing loose. Repeat up to 3 times daily

Other information

- Store at room temperature

Inactive ingredients:

cedar leaf oil, nutmeg oil, paraffin, patrolatum, thymol, turpentine oil

PACKAGE LABEL

Medicated chest rub

4 oz (113 g)